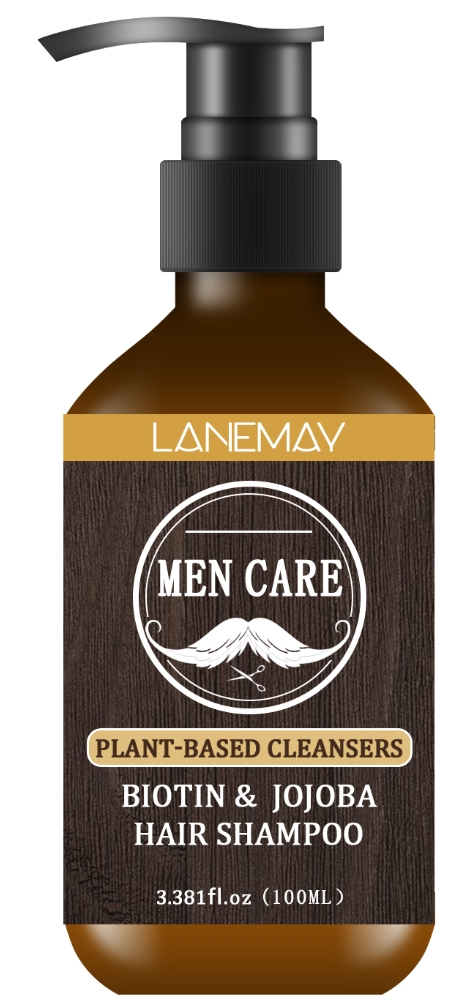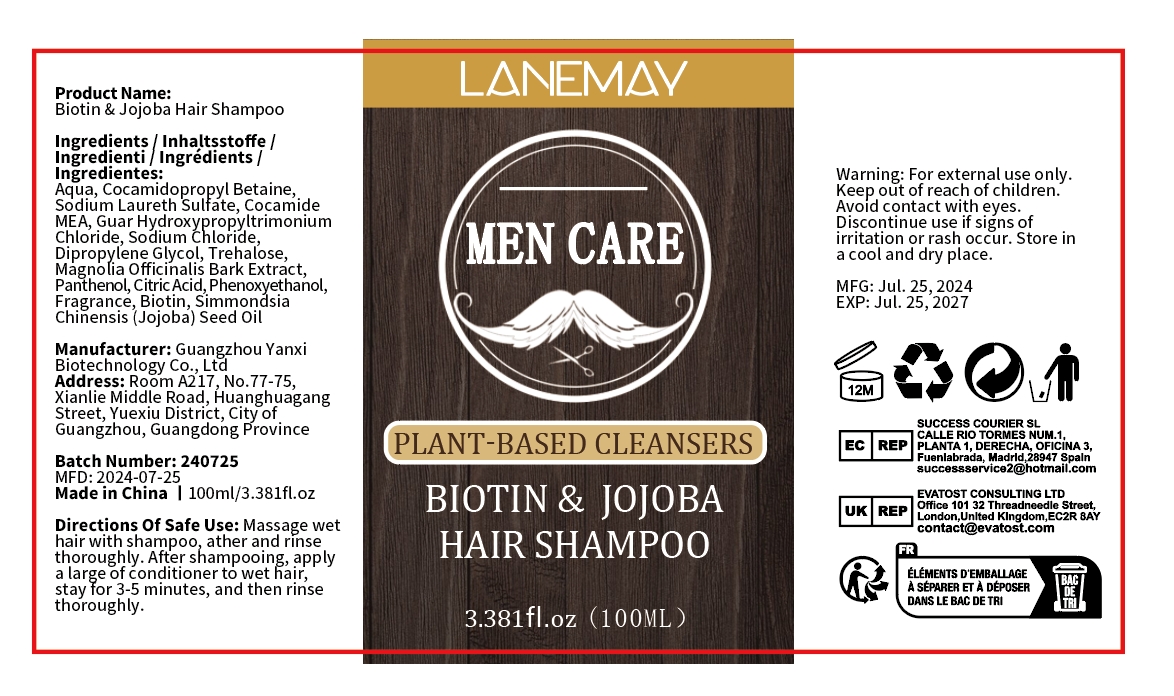 DRUG LABEL: Biotin Jojoba HairShampoo
NDC: 84025-177 | Form: SHAMPOO
Manufacturer: Guangzhou Yanxi Biotechnology Co.. Ltd
Category: otc | Type: HUMAN OTC DRUG LABEL
Date: 20240827

ACTIVE INGREDIENTS: COCAMIDOPROPYL BETAINE 5 mg/100 mL; DIPROPYLENE GLYCOL 3 mg/100 mL
INACTIVE INGREDIENTS: WATER

WARNINGS

Keep out of children

DOSAGE AND ADMINISTRATION

Shampoo And Conditioner for keeping hair and scalp healthy

INACTIVE INGREDIENT

AQUA

INDICATIONS AND USAGE

For daily hair care

Keep out of children

PURPOSE

Effectively cleans and nourishes hair